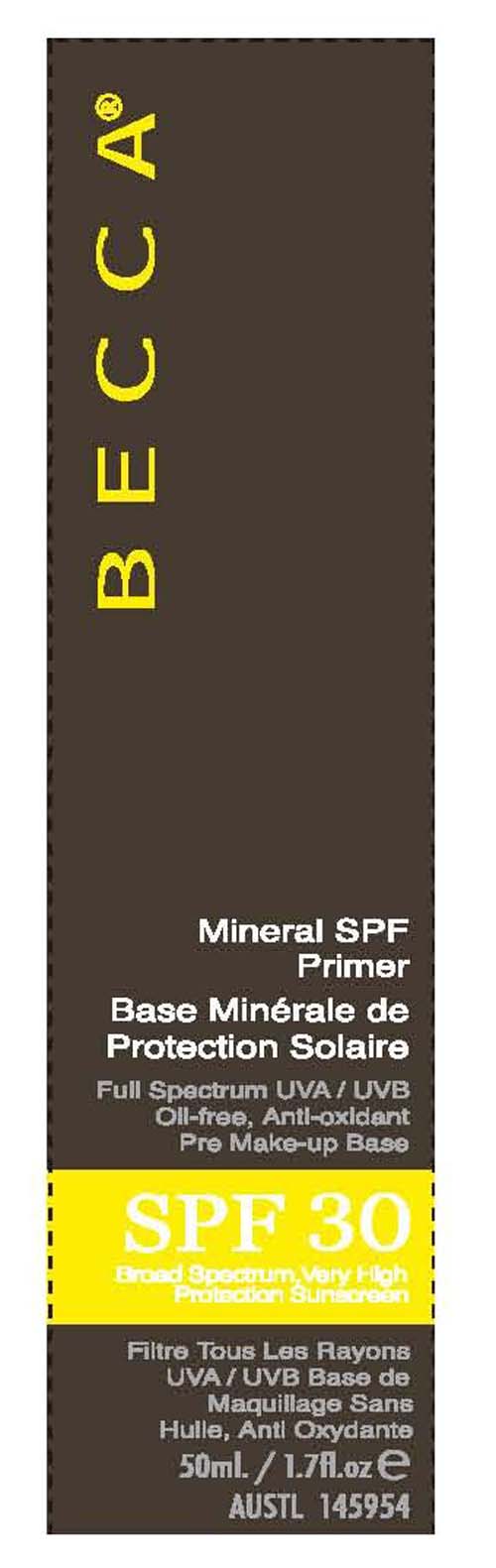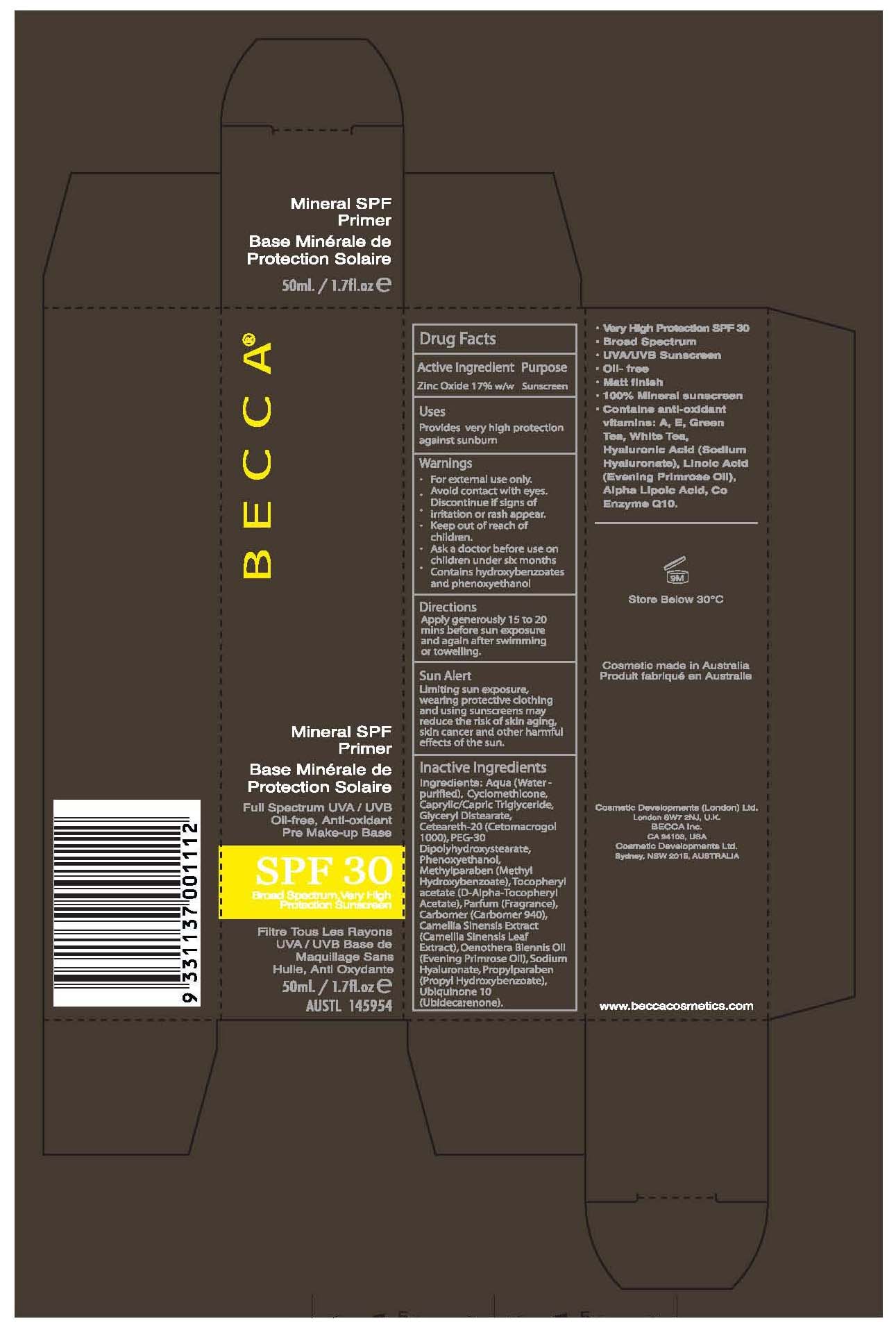 DRUG LABEL: Becca
NDC: 23104-5010 | Form: CREAM
Manufacturer: Cosmetic Developments Limited
Category: otc | Type: HUMAN OTC DRUG LABEL
Date: 20100708

ACTIVE INGREDIENTS: ZINC OXIDE 17 mL/100 mL

Mineral SPF30 Primer

Active Ingredients Purpose

Zinc Oxide 17% Sunscreen

Warnings

-For external use only.

-Avoid contact with eyes.

-Discontinue if signs of irritation or rash appear

-Keep out of reach of children

-Ask a doctor before use on children under six months

-Contains hydroxybenzoates and phenoxyethanol

Uses
-Provides very high protection against sunburn

Directions
-Apply generously 15 to 20 mins before sun exposure and again after swimming or toweling

GENERAL PRECAUTIONS

Sun Alert: Limiting sun exposure, wearing protective clothing and using sunscreens may reduce the risk of skin aging, skin cancer and other harmful effects of the sun.

INACTIVE INGREDIENT

Inactive Ingredients: Aqua (water-purified), Cyclomethicone, Caprylic/Capric Triglyceride, Glyceryl Distearate, Ceteareth-20 (Cetomacrogol 1000), PEG-30 Dipolyhydroxystearate, Phenoxyethanol, Methylparaben (Methyl Hydroxybenzoate), Tocopheryl acetate (D-Alpha-Tocopheryl Acetate), Parfum (Fragrance), Carbomer (Carbomer 940), Camellia Sinensis Extract (Camellia Sinensis Leaf Extract, Oenothera Biennis Oil (Evening Primrose Oil), Sodium Hyaluronate, Propylparaben (Propyl Hydroxybenzoate), Ubiquinone 10 (Ubidecarenone).

PACKAGE LABEL

Becca

Mineral SPF Primer

SPF 30

50 ml. / 1.7 fl.oz